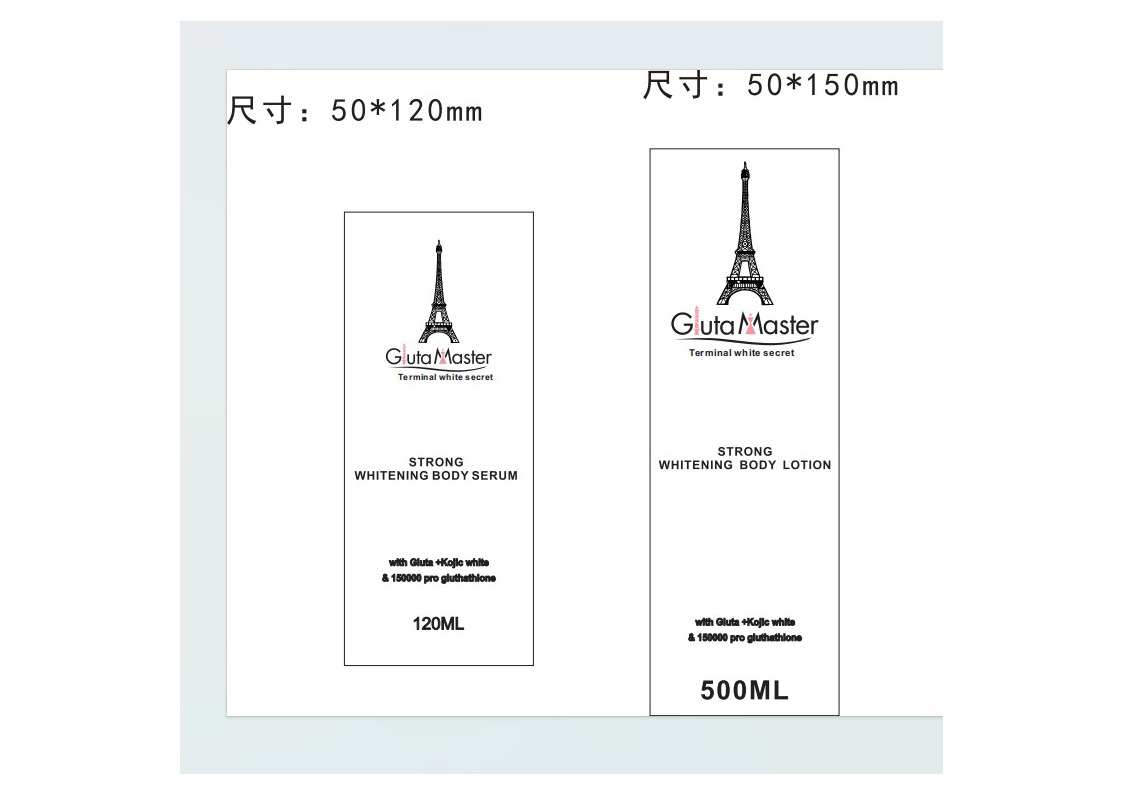 DRUG LABEL: strong whitening bodylotion
NDC: 84423-045 | Form: EMULSION
Manufacturer: Guangzhou Kadiya Biotechnology Co., Ltd.
Category: otc | Type: HUMAN OTC DRUG LABEL
Date: 20240828

ACTIVE INGREDIENTS: GLUTATHIONE 2.5 mg/500 mL; NIACINAMIDE 10 mg/500 mL; ASCORBIC ACID 5 mg/500 mL; KOJIC ACID 2.5 mg/500 mL
INACTIVE INGREDIENTS: WATER; CETOSTEARYL ALCOHOL; UREA; PEG-100 STEARATE; GLYCERIN; C13-16 ISOPARAFFIN; DIMETHICONE; DMDM HYDANTOIN; IODOPROPYNYL BUTYLCARBAMATE; CARBOMER HOMOPOLYMER, UNSPECIFIED TYPE; ALLANTOIN; TROLAMINE; PROPYLPARABEN; GLYCERYL MONOSTEARATE; MINERAL OIL; POLYOXYL 20 CETOSTEARYL ETHER; METHYLPARABEN; POTASSIUM CETYL PHOSPHATE; EDETATE DISODIUM; 3-O-ETHYL ASCORBIC ACID; BUTYLENE GLYCOL

PURPOSE

For facial skin cleansing, exfoliation and whitening moisturization

INACTIVE INGREDIENT

For facial skin cleansing, exfoliation and whitening moisturization

WARNINGS

1、For external use only, avoid contact with eyes when used
2、Keep out of reach of children

INDICATIONS AND USAGE

For facial skin cleansing, exfoliation and whitening moisturization

DOSAGE AND ADMINISTRATION

For facial skin cleansing, exfoliation and whitening moisturization

Active Ingredients
NIACINAMIDE2%
Glutathione0.5%
KOJIC ACID0.5%
ASCORBIC ACID1%

KEEP OUT OF REACH OF CHILDREN SECTION

PACKAGE LABEL

Active Ingredients
NIACINAMIDE2%
Glutathione0.5%
KOJIC ACID0.5%
ASCORBIC ACID1%

Uses：
For facial skin cleansing, exfoliation and whitening moisturization
The storage method：
Store sealed in a cool place and out of sunlight

Warning.
1、For external use only, avoid contact with eyes when used
2、Keep out of reach of children

Inactive ingredients：
AQUA、MINERAL OIL、GLYCERIN、CETEARYL ALCOHOL、UREA、、GLYCERYL STEARATE、PEG-100 STEARATE、CETEARETH-20、POTASSIUM CETYL PHOSPHATE、C13-16 ISOPARAFFIN、DIMETHICONE、、DMDM HYDANTOIN、BUTYLENE GLYCOL、IODOPROPYNYL BUTYLCARBAMATE、AROMA、METHYLPARABEN、CARBOMER、ALLANTOIN、TRIETHANOLAMINE、PROPYLPARABEN、DISODIUM EDTA、3-o-ETHYL、ASCORBIC ACID